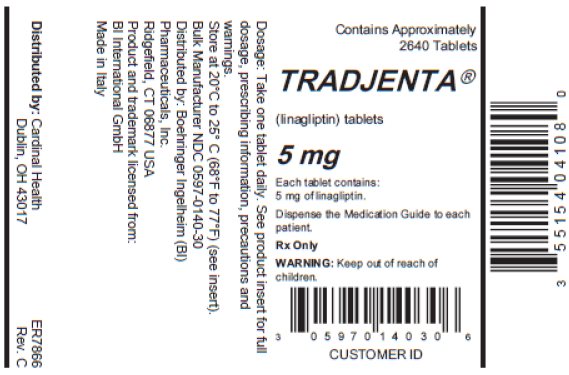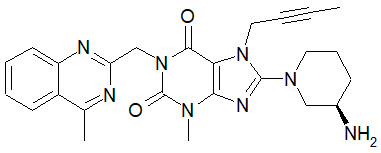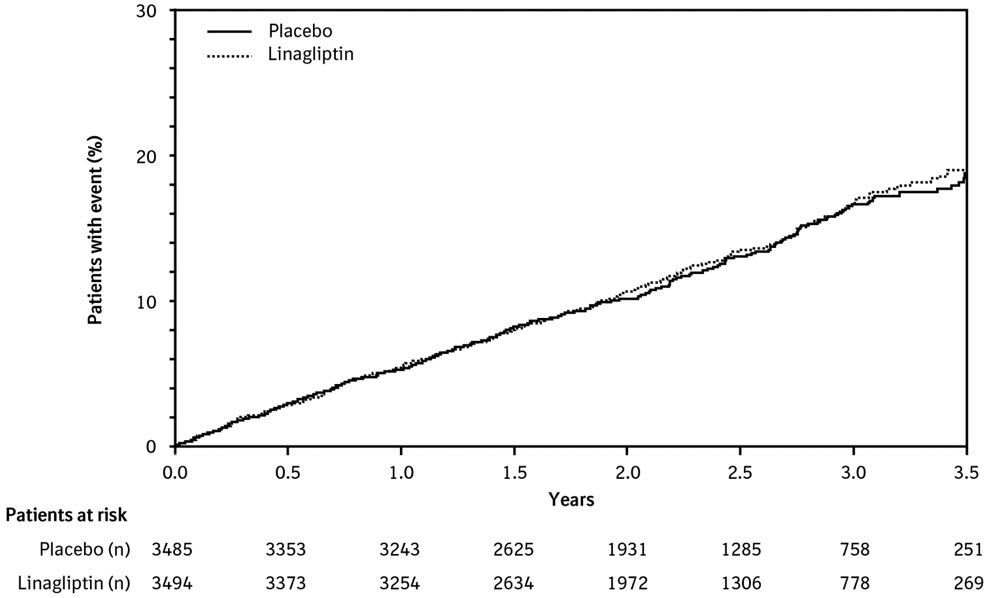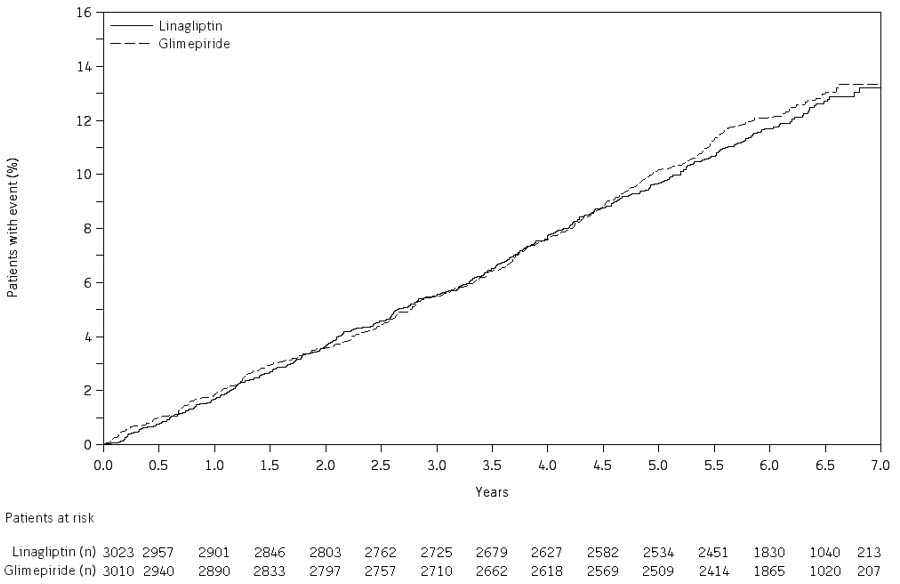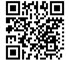 DRUG LABEL: Tradjenta
NDC: 55154-0410 | Form: TABLET, FILM COATED
Manufacturer: Cardinal Health 107, LLC
Category: prescription | Type: HUMAN PRESCRIPTION DRUG LABEL
Date: 20250827

ACTIVE INGREDIENTS: LINAGLIPTIN 5 mg/1 1
INACTIVE INGREDIENTS: COPOVIDONE K25-31; STARCH, CORN; MAGNESIUM STEARATE; MANNITOL; HYPROMELLOSE, UNSPECIFIED; POLYETHYLENE GLYCOL, UNSPECIFIED; FERRIC OXIDE RED; TALC; TITANIUM DIOXIDE

HIGHLIGHTS OF PRESCRIBING INFORMATION

These highlights do not include all the information needed to use TRADJENTA safely and effectively. See full prescribing information for TRADJENTA.
TRADJENTA® (linagliptin tablets), for oral use
Initial U.S. Approval: 2011

1 INDICATIONS AND USAGE

TRADJENTA is a dipeptidyl peptidase-4 (DPP-4) inhibitor indicated as an adjunct to diet and exercise to improve glycemic control in adults with type 2 diabetes mellitus (1)

Limitations of Use

- Not recommended in patients with type 1 diabetes mellitus as it would not be effective (1)
- Has not been studied in patients with a history of pancreatitis (1)

2 DOSAGE AND ADMINISTRATION

- The recommended dosage of TRADJENTA is 5 mg orally once daily (2.1)
- TRADJENTA can be taken with or without food (2.1)

3 DOSAGE FORMS AND STRENGTHS

Tablets: 5 mg (3)

4 CONTRAINDICATIONS

Hypersensitivity to linagliptin or any of the excipients in TRADJENTA (4, 5.3)

5 WARNINGS AND PRECAUTIONS

- Pancreatitis: There have been reports of acute pancreatitis, including fatal pancreatitis. If pancreatitis is suspected, promptly discontinue TRADJENTA. (5.1)
- Hypoglycemia: Consider lowering the dosage of insulin secretagogue or insulin to reduce the risk of hypoglycemia when initiating TRADJENTA (5.2)
- Hypersensitivity reactions: Serious hypersensitivity reactions (e.g., anaphylaxis, angioedema, and exfoliative skin conditions) have occurred with TRADJENTA. If hypersensitivity reactions occur, discontinue TRADJENTA, treat promptly, and monitor until signs and symptoms resolve. (5.3)
- Arthralgia: Severe and disabling arthralgia has been reported in patients taking TRADJENTA. Consider as a possible cause for severe joint pain and discontinue drug if appropriate. (5.4)
- Bullous pemphigoid: There have been reports of bullous pemphigoid requiring hospitalization. Tell patients to report development of blisters or erosions. If bullous pemphigoid is suspected, discontinue TRADJENTA. (5.5)
- Heart failure: Heart failure has been observed with two other members of the DPP-4 inhibitor class. Consider risks and benefits of TRADJENTA in patients who have known risk factors for heart failure. Monitor for signs and symptoms. (5.6)

6 ADVERSE REACTIONS

Most common adverse reaction (incidence ≥5% and more often than placebo) was nasopharyngitis (6.1)

To report SUSPECTED ADVERSE REACTIONS, contact Boehringer Ingelheim Pharmaceuticals, Inc. at 1-800-542-6257, or FDA at 1-800-FDA-1088 or www.fda.gov/medwatch.

7 DRUG INTERACTIONS

Strong P-glycoprotein/CYP3A4 inducer: The efficacy of TRADJENTA may be reduced when administered in combination (e.g., with rifampin). Use of alternative treatments is strongly recommended. (7.1)

FULL PRESCRIBING INFORMATION

1 INDICATIONS AND USAGE

TRADJENTA is indicated as an adjunct to diet and exercise to improve glycemic control in adults with type 2 diabetes mellitus.

Limitations of Use

TRADJENTA is not recommended in patients with type 1 diabetes mellitus as it would not be effective.

TRADJENTA has not been studied in patients with a history of pancreatitis. It is unknown whether patients with a history of pancreatitis are at an increased risk for the development of pancreatitis while using TRADJENTA [see Warnings and Precautions (5.1)].

2 DOSAGE AND ADMINISTRATION

2.1 Recommended Dosage and Administration

The recommended dosage of TRADJENTA is 5 mg taken orally once daily, with or without food.

3 DOSAGE FORMS AND STRENGTHS

Tablets: 5 mg, light red, round, biconvex, bevel-edged, film-coated tablets with "D5" debossed on one side and the Boehringer Ingelheim symbol debossed on the other side.

4 CONTRAINDICATIONS

TRADJENTA is contraindicated in patients with hypersensitivity to linagliptin or any of the excipients in TRADJENTA, reactions such as anaphylaxis, angioedema, exfoliative skin conditions, urticaria, or bronchial hyperreactivity have occurred [see Warnings and Precautions (5.3) and Adverse Reactions (6)].

5 WARNINGS AND PRECAUTIONS

5.1 Pancreatitis

Acute pancreatitis, including fatal pancreatitis, has been reported in patients treated with TRADJENTA. In the CARMELINA trial [see Clinical Studies (14.2)], acute pancreatitis was reported in 9 (0.3%) patients treated with TRADJENTA and in 5 (0.1%) patients treated with placebo. Two patients treated with TRADJENTA in the CARMELINA trial had acute pancreatitis with a fatal outcome. There have been postmarketing reports of acute pancreatitis, including fatal pancreatitis, in patients treated with TRADJENTA.

Take careful notice of potential signs and symptoms of pancreatitis. If pancreatitis is suspected, promptly discontinue TRADJENTA and initiate appropriate management. It is unknown whether patients with a history of pancreatitis are at increased risk for the development of pancreatitis while using TRADJENTA.

5.2 Hypoglycemia with Concomitant Use with Insulin and Insulin Secretagogues

Insulin secretagogues and insulin are known to cause hypoglycemia. The risk of hypoglycemia is increased when TRADJENTA is used in combination with an insulin secretagogue (e.g., sulfonylurea) or insulin [see Adverse Reactions (6.1)]. The use of TRADJENTA in combination with insulin in subjects with severe renal impairment was associated with a higher rate of hypoglycemia [see Adverse Reactions (6.1)]. Therefore, a lower dosage of the insulin secretagogue or insulin may be required to reduce the risk of hypoglycemia when used in combination with TRADJENTA.

5.3 Hypersensitivity Reactions

There have been postmarketing reports of serious hypersensitivity reactions in patients treated with TRADJENTA. These reactions include anaphylaxis, angioedema, and exfoliative skin conditions. Onset of these reactions occurred predominantly within the first 3 months after initiation of treatment with TRADJENTA, with some reports occurring after the first dose. If a serious hypersensitivity reaction is suspected, discontinue TRADJENTA, assess for other potential causes for the event, and institute alternative treatment for diabetes mellitus.

Angioedema has also been reported with other dipeptidyl peptidase-4 (DPP-4) inhibitors. Use caution in a patient with a history of angioedema to another DPP-4 inhibitor because it is unknown whether such patients will be predisposed to angioedema with TRADJENTA.

5.4 Severe and Disabling Arthralgia

There have been postmarketing reports of severe and disabling arthralgia in patients taking TRADJENTA [see Adverse Reactions (6)]. The time to onset of symptoms following initiation of drug therapy varied from one day to years. Patients experienced relief of symptoms upon discontinuation of the medication. A subset of patients experienced a recurrence of symptoms when restarting the same drug or a different DPP-4 inhibitor. Consider the drug as a possible cause for severe joint pain and discontinue drug if appropriate.

5.5 Bullous Pemphigoid

Bullous pemphigoid was reported in 7 (0.2%) patients treated with TRADJENTA compared to none in patients treated with placebo in the CARMELINA trial [see Clinical Studies (14.2)], and 3 of these patients were hospitalized due to bullous pemphigoid. Postmarketing cases of bullous pemphigoid requiring hospitalization have been reported with DPP-4 inhibitor use. In reported cases, patients typically recovered with topical or systemic immunosuppressive treatment and discontinuation of the DPP-4 inhibitor. Tell patients to report development of blisters or erosions while receiving TRADJENTA. If bullous pemphigoid is suspected, TRADJENTA should be discontinued and referral to a dermatologist should be considered for diagnosis and appropriate treatment.

5.6 Heart Failure

An association between DPP-4 inhibitor treatment and heart failure has been observed in cardiovascular outcomes trials for two other members of the DPP-4 inhibitor class. These trials evaluated patients with type 2 diabetes mellitus and atherosclerotic cardiovascular disease.

Consider the risks and benefits of TRADJENTA prior to initiating treatment in patients at risk for heart failure, such as those with a prior history of heart failure and a history of renal impairment, and observe these patients for signs and symptoms of heart failure during therapy. Advise patients of the characteristic symptoms of heart failure and to immediately report such symptoms. If heart failure develops, evaluate and manage according to current standards of care and consider discontinuation of TRADJENTA.

6 ADVERSE REACTIONS

The following serious adverse reactions are described below or elsewhere in the prescribing information:

- Pancreatitis [see Warnings and Precautions (5.1)]
- Hypoglycemia with Concomitant Use with Insulin and Insulin Secretagogues [see Warnings and Precautions (5.2)]
- Hypersensitivity Reactions [see Warnings and Precautions (5.3)]
- Severe and Disabling Arthralgia [see Warnings and Precautions (5.4)]
- Bullous Pemphigoid [see Warnings and Precautions (5.5)]
- Heart Failure [see Warnings and Precautions (5.6)]

6.1 Clinical Trials Experience

Because clinical trials are conducted under widely varying conditions, adverse reaction rates observed in the clinical trials of a drug cannot be directly compared to rates in the clinical trials of another drug and may not reflect the rates observed in practice.

The safety evaluation of TRADJENTA 5 mg once daily in patients with type 2 diabetes mellitus is based on 14 placebo-controlled trials, 1 active-controlled trial, and one trial in patients with severe renal impairment. In the 14 placebo-controlled studies, a total of 3,625 patients were randomized and treated with TRADJENTA 5 mg daily and 2,176 with placebo. The mean exposure in patients treated with TRADJENTA across studies was 29.6 weeks. The maximum follow-up was 78 weeks.

TRADJENTA 5 mg once daily was studied as monotherapy in three placebo-controlled trials of 18 and 24 weeks' duration and in five additional placebo-controlled studies lasting ≤18 weeks. The use of TRADJENTA in combination with other antihyperglycemic agents was studied in six placebo-controlled trials: two with metformin (12 and 24 weeks' treatment duration); one with a sulfonylurea (18 weeks' treatment duration); one with metformin and sulfonylurea (24 weeks' treatment duration); one with pioglitazone (24 weeks' treatment duration); and one with insulin (primary endpoint at 24 weeks).

In a pooled dataset of 14 placebo-controlled clinical trials, adverse reactions that occurred in ≥2% of patients receiving TRADJENTA (n = 3,625) and more commonly than in patients given placebo (n = 2,176), are shown in Table 1.

Table 1 Adverse Reactions Reported in ≥2% of Patients Treated with TRADJENTA and Greater than Placebo in Placebo-Controlled Clinical Studies of TRADJENTA Monotherapy or Combination Therapy
Adverse Reactions | TRADJENTA 5 mg (%) n = 3,625 | Placebo (%) n = 2,176
Nasopharyngitis | 7.0 | 6.1
Diarrhea | 3.3 | 3.0
Cough | 2.1 | 1.4

Rates for other adverse reactions for TRADJENTA 5 mg vs placebo when TRADJENTA was used in combination with specific antidiabetic agents were: urinary tract infection (3.1% vs 0%) and hypertriglyceridemia (2.4% vs 0%) when TRADJENTA was used as add-on to sulfonylurea; hyperlipidemia (2.7% vs 0.8%) and weight increased (2.3% vs 0.8%) when TRADJENTA was used as add-on to pioglitazone; and constipation (2.1% vs 1%) when TRADJENTA was used as add-on to basal insulin therapy. Other adverse reactions reported in clinical studies with treatment of TRADJENTA were hypersensitivity (e.g., urticaria, angioedema, localized skin exfoliation, or bronchial hyperreactivity) and myalgia.

Following 104 weeks' treatment in a controlled trial comparing TRADJENTA with glimepiride in which all patients were also receiving metformin, adverse reactions reported in ≥5% of patients treated with TRADJENTA (n = 776) and more frequently than in patients treated with a sulfonylurea (n = 775) were back pain (9.1% vs 8.4%), arthralgia (8.1% vs 6.1%), upper respiratory tract infection (8.0% vs 7.6%), headache (6.4% vs 5.2%), cough (6.1% vs 4.9%), and pain in extremity (5.3% vs 3.9%).

In the clinical trial program, pancreatitis was reported in 15.2 cases per 10,000 patient year exposure while being treated with TRADJENTA compared with 3.7 cases per 10,000 patient year exposure while being treated with comparator (placebo and active comparator, sulfonylurea). Three additional cases of pancreatitis were reported following the last administered dose of linagliptin.

Other Adverse Reactions

Hypoglycemia

Table 2 summarizes the incidence of hypoglycemia in placebo-controlled studies of TRADJENTA. The incidence of hypoglycemia increased when TRADJENTA was administered with sulfonylurea or insulin.

Table 2 Incidence (%) of Hypoglycemia in Placebo-Controlled Clinical Studies of TRADJENTA in Patients with Type 2 Diabetes Mellitus
Add-on to Sulfonylurea (18 Weeks) | Placebo (N=84) | TRADJENTA (N=161)
Hypoglycemia with plasma glucose <54 mg/dL (%) | 1.2 | 1.9
Severe* hypoglycemia (%) | 0 | 0
Add-on to Metformin and Sulfonylurea (24 Weeks) | Placebo (N=263) | TRADJENTA (N=792)
Hypoglycemia with plasma glucose <54 mg/dL (%) | 5.3 | 8.1
Severe* hypoglycemia (%) | 0.8 | 0.6
Add-on to Basal Insulin (52 Weeks) | Placebo (N=630) | TRADJENTA (N=631)
Hypoglycemia with plasma glucose <54 mg/dL (%) | 21.6 | 19.8
Severe* hypoglycemia (%) | 1.1 | 1.7
*Hypoglycemia requiring assistance of another person to actively administer carbohydrate, glucagon, or other resuscitative actions.

In an active-controlled (glimepiride) cardiovascular safety trial with TRADJENTA (CAROLINA) with median time on treatment of 5.9 years, the incidence of severe hypoglycemia was 0.3% in the TRADJENTA group (N=3,014) and 2.2% in glimepiride group (N=3,000).

Use in Renal Impairment

TRADJENTA was compared to placebo as add-on to pre-existing antidiabetic therapy over 52 weeks in 133 patients with severe renal impairment (estimated GFR <30 mL/min). For the initial 12 weeks of the trial, background antidiabetic therapy was kept stable and included insulin, sulfonylurea, glinides, and pioglitazone. For the remainder of the trial, dosage adjustments in antidiabetic background therapy were allowed.

In general, the incidence of adverse events including severe hypoglycemia was similar to those reported in other TRADJENTA trials. The observed incidence of hypoglycemia was higher (TRADJENTA, 63% compared to placebo, 49%) due to an increase in asymptomatic hypoglycemic events especially during the first 12 weeks when background glycemic therapies were kept stable. Ten TRADJENTA-treated patients (15%) and 11 placebo-treated patients (17%) reported at least one episode of confirmed symptomatic hypoglycemia (accompanying finger stick glucose ≤54 mg/dL). During the same time period, severe hypoglycemic events, defined as an event requiring the assistance of another person to actively administer carbohydrate, glucagon or other resuscitative actions, were reported in 3 (4.4%) TRADJENTA-treated patients and 3 (4.6%) placebo-treated patients. Events that were considered life-threatening or required hospitalization were reported in 2 (2.9%) patients on TRADJENTA and 1 (1.5%) patient on placebo.

Renal function as measured by mean eGFR and creatinine clearance did not change over 52 weeks' treatment compared to placebo.

Laboratory Test Abnormalities in Clinical Trials

Changes in laboratory findings were similar in patients treated with TRADJENTA 5 mg compared to patients treated with placebo.

Increase in Uric Acid: Changes in laboratory values that occurred more frequently in the TRADJENTA group and ≥1% more than in the placebo group were increases in uric acid (1.3% in the placebo group, 2.7% in the TRADJENTA group).

Increase in Lipase: In a placebo-controlled clinical trial with TRADJENTA in type 2 diabetes mellitus patients with micro- or macroalbuminuria, a mean increase of 30% in lipase concentrations from baseline to 24 weeks was observed in the TRADJENTA arm compared to a mean decrease of 2% in the placebo arm. Lipase levels above 3 times upper limit of normal were seen in 8.2% compared to 1.7% patients in the TRADJENTA and placebo arms, respectively.

Increase in Amylase: In a cardiovascular safety trial comparing TRADJENTA versus glimepiride in patients with type 2 diabetes mellitus, amylase levels above 3 times upper limit of normal were seen in 1.0% compared to 0.5% of patients in the TRADJENTA and glimepiride arms, respectively.

The clinical significance of elevations in lipase and amylase with TRADJENTA is unknown in the absence of potential signs and symptoms of pancreatitis [see Warnings and Precautions (5.1)].

Vital Signs

No clinically meaningful changes in vital signs were observed in patients treated with TRADJENTA.

6.2 Postmarketing Experience

Additional adverse reactions have been identified during postapproval use of TRADJENTA. Because these reactions are reported voluntarily from a population of uncertain size, it is generally not possible to reliably estimate their frequency or establish a causal relationship to drug exposure.

- Gastrointestinal Disorders: Acute pancreatitis, including fatal pancreatitis [see Indications and Usage (1)], mouth ulceration, stomatitis
- Immune System Disorders: Hypersensitivity reactions including anaphylaxis, angioedema, and exfoliative skin conditions
- Musculoskeletal and Connective Tissue Disorders: Rhabdomyolysis, severe and disabling arthralgia
- Skin and Subcutaneous Tissue Disorders: Bullous pemphigoid, rash

7 DRUG INTERACTIONS

7.1 Inducers of P-glycoprotein or CYP3A4 Enzymes

Rifampin decreased linagliptin exposure, suggesting that the efficacy of TRADJENTA may be reduced when administered in combination with a strong P-gp or CYP3A4 inducer. Therefore, use of alternative treatments is strongly recommended when linagliptin is to be administered with a strong P-gp or CYP3A4 inducer [see Clinical Pharmacology (12.3)].

7.2 Insulin Secretagogues or Insulin

Insulin and insulin secretagogues are known to cause hypoglycemia. The risk of hypoglycemia is increased when linagliptin is used in combination with an insulin secretagogue (e.g., sulfonylurea) or insulin. Coadministration of TRADJENTA with an insulin secretagogue (e.g., sulfonylurea) or insulin may require lower dosages of the insulin secretagogue or insulin to reduce the risk of hypoglycemia [see Warnings and Precautions (5.2)].

8 USE IN SPECIFIC POPULATIONS

8.1 Pregnancy

Risk Summary

The limited data with TRADJENTA use in pregnant women are not sufficient to inform of drug-associated risk for major birth defects and miscarriage. There are risks to the mother and fetus associated with poorly controlled diabetes in pregnancy [see Clinical Considerations].

In animal reproduction studies, no adverse developmental effects were observed when linagliptin was administered to pregnant rats during the period of organogenesis at doses similar to the maximum recommended clinical dose, based on exposure [see Data].

The estimated background risk of major birth defects is 6% to 10% in women with pre-gestational diabetes with a HbA1c >7 and has been reported to be as high as 20% to 25% in women with HbA1c >10. The estimated background risk of miscarriage for the indicated population is unknown. In the U.S. general population, the estimated background risk of major birth defects and miscarriage in clinically recognized pregnancies is 2% to 4% and 15% to 20%, respectively.

Clinical Considerations

Disease-associated maternal and/or embryo/fetal risk

Poorly controlled diabetes in pregnancy increases the maternal risk for diabetic ketoacidosis, preeclampsia, spontaneous abortions, preterm delivery, and delivery complications. Poorly controlled diabetes increases the fetal risk for major birth defects, stillbirth, and macrosomia related morbidity.

Data

Animal Data

No adverse developmental outcome was observed when linagliptin was administered to pregnant Wistar Han rats and Himalayan rabbits during the period of organogenesis at doses up to 240 mg/kg/day and 150 mg/kg/day, respectively. These doses represent approximately 943-times (rats) and 1,943-times (rabbits) the 5 mg maximum clinical dose, based on exposure. No adverse functional, behavioral, or reproductive outcome was observed in offspring following administration of linagliptin to Wistar Han rats from gestation day 6 to lactation day 21 at a dose 49-times the maximum recommended human dose, based on exposure.

Linagliptin crosses the placenta into the fetus following oral dosing in pregnant rats and rabbits.

8.2 Lactation

Risk Summary

There is no information regarding the presence of linagliptin in human milk, the effects on the breastfed infant, or the effects on milk production. However, linagliptin is present in rat milk. Therefore, the developmental and health benefits of breastfeeding should be considered along with the mother's clinical need for TRADJENTA and any potential adverse effects on the breastfed child from TRADJENTA or from the underlying maternal condition.

8.4 Pediatric Use

The safety and effectiveness of TRADJENTA have not been established in pediatric patients.

Effectiveness of TRADJENTA was not demonstrated in a 26-week randomized, double-blind, placebo-controlled trial (NCT03429543) in 157 pediatric patients aged 10 to 17 years with inadequately controlled type 2 diabetes mellitus.

8.5 Geriatric Use

In linagliptin studies, 1,085 linagliptin-treated patients were 65 years of age and older and 131 patients were 75 years of age and older. In these linagliptin studies, no overall differences in safety or effectiveness of linagliptin were observed between geriatric patients and younger adult patients.

8.6 Renal Impairment

No dosage adjustment is recommended for patients with renal impairment [see Clinical Pharmacology (12.3)].

In the TRADJENTA treatment arm of the CARMELINA trial [see Clinical Studies (14)], 2,200 (63%) patients had renal impairment (eGFR <60 mL/min/1.73 m^2). Approximately 20% of the population had eGFR ≥45 to <60 mL/min/1.73 m^2, 28% of the population had eGFR ≥30 to <45 mL/min/1.73 m^2 and 15% had eGFR <30 mL/min/1.73 m^2. The overall incidence of adverse reactions were generally similar between the TRADJENTA and placebo treatment arms.

8.7 Hepatic Impairment

No dose adjustment is recommended for patients with hepatic impairment [see Clinical Pharmacology (12.3)].

10 OVERDOSAGE

In the event of an overdose with TRADJENTA, consider contacting the Poison Help Line (1-800-222-1222) or a medical toxicologist for additional overdosage management recommendations. Removal of linagliptin by hemodialysis or peritoneal dialysis is unlikely.

11 DESCRIPTION

TRADJENTA tablets for oral use contain linagliptin, an inhibitor of the DPP-4 enzyme.

The chemical name of linagliptin is 1H-Purine-2,6-dione, 8-[(3R)-3-amino-1-piperidinyl]-7-(2-butyn-1-yl)-3,7-dihydro-3-methyl-1-[(4-methyl-2-quinazolinyl)methyl]-

The molecular formula is C25H28N8O2 and the molecular weight is 472.54 g/mol. The structural formula is:

Linagliptin is a white to yellowish, not or only slightly hygroscopic solid substance. It is very slightly soluble in water (0.9 mg/mL). Linagliptin is soluble in methanol (ca. 60 mg/mL), sparingly soluble in ethanol (ca. 10 mg/mL), very slightly soluble in isopropanol (<1 mg/mL), and very slightly soluble in acetone (ca. 1 mg/mL).

Each film-coated tablet of TRADJENTA contains 5 mg of linagliptin free base and the following inactive ingredients: copovidone, corn starch, magnesium stearate, mannitol, and pregelatinized starch. In addition, the film coating contains the following inactive ingredients: hypromellose, polyethylene glycol, red ferric oxide, talc, and titanium dioxide.

12 CLINICAL PHARMACOLOGY

12.1 Mechanism of Action

Linagliptin is an inhibitor of DPP-4, an enzyme that degrades the incretin hormones glucagon-like peptide-1 (GLP-1) and glucose-dependent insulinotropic polypeptide (GIP). Thus, linagliptin increases the concentrations of active incretin hormones, stimulating the release of insulin in a glucose-dependent manner and decreasing the levels of glucagon in the circulation. Both incretin hormones are involved in the physiological regulation of glucose homeostasis. Incretin hormones are secreted at a low basal level throughout the day and levels rise immediately after meal intake. GLP-1 and GIP increase insulin biosynthesis and secretion from pancreatic beta cells in the presence of normal and elevated blood glucose levels. Furthermore, GLP-1 also reduces glucagon secretion from pancreatic alpha-cells, resulting in a reduction in hepatic glucose output.

12.2 Pharmacodynamics

Linagliptin binds to DPP-4 in a reversible manner and thus increases the concentrations of incretin hormones. Linagliptin glucose-dependently increases insulin secretion and lowers glucagon secretion, thus resulting in better regulation of glucose homeostasis. Linagliptin binds selectively to DPP-4 and selectively inhibits DPP-4, but not DPP-8 or DPP-9 activity in vitro at concentrations approximating therapeutic exposures.

Cardiac Electrophysiology

In a randomized, placebo-controlled, active-comparator, 4-way crossover study, 36 healthy subjects were administered a single oral dose of linagliptin 5 mg, linagliptin 100 mg (20 times the recommended dose), moxifloxacin, and placebo. No increase in QTc was observed with either the recommended dose of 5 mg or the 100 mg dose. At the 100 mg dose, peak linagliptin plasma concentrations were approximately 38-fold higher than the peak concentrations following a 5 mg dose.

12.3 Pharmacokinetics

The pharmacokinetics of linagliptin has been characterized in healthy subjects and patients with type 2 diabetes mellitus. After oral administration of a single 5 mg dose to healthy subjects, peak plasma concentrations of linagliptin occurred at approximately 1.5 hours post dose (Tmax); the mean plasma area under the curve (AUC) was 139 nmol*h/L and maximum concentration (Cmax) was 8.9 nmol/L.

Plasma concentrations of linagliptin decline in at least a biphasic manner with a long terminal half-life (>100 hours), related to the saturable binding of linagliptin to DPP-4. The prolonged elimination phase does not contribute to the accumulation of the drug. The effective half-life for accumulation of linagliptin, as determined from oral administration of multiple doses of linagliptin 5 mg, is approximately 12 hours. After once-daily dosing, steady-state plasma concentrations of linagliptin 5 mg are reached by the third dose, and Cmax and AUC increased by a factor of 1.3 at steady-state compared with the first dose. The intra-subject and inter-subject coefficients of variation for linagliptin AUC were small (12.6% and 28.5%, respectively). Plasma AUC of linagliptin increased in a less than dose-proportional manner in the dose range of 1 to 10 mg. The pharmacokinetics of linagliptin is similar in healthy subjects and in patients with type 2 diabetes mellitus.

Absorption

The absolute bioavailability of linagliptin is approximately 30%. A high-fat meal reduced Cmax by 15% and increased AUC by 4%; this effect is not clinically relevant. TRADJENTA may be administered with or without food.

Distribution

The mean apparent volume of distribution at steady-state following a single intravenous dose of linagliptin 5 mg to healthy subjects is approximately 1,110 L, indicating that linagliptin extensively distributes to the tissues. Plasma protein binding of linagliptin is concentration-dependent, decreasing from about 99% at 1 nmol/L to 75%-89% at ≥30 nmol/L, reflecting saturation of binding to DPP-4 with increasing concentration of linagliptin. At high concentrations, where DPP-4 is fully saturated, 70% to 80% of linagliptin remains bound to plasma proteins and 20% to 30% is unbound in plasma. Plasma binding is not altered in patients with renal or hepatic impairment.

Elimination

Linagliptin has a terminal half-life of about 200 hours at steady-state, though the accumulation half-life is about 11 hours. Renal clearance at steady-state was approximately 70 mL/min.

Metabolism

Following oral administration, the majority (about 90%) of linagliptin is excreted unchanged, indicating that metabolism represents a minor elimination pathway. A small fraction of absorbed linagliptin is metabolized to a pharmacologically inactive metabolite, which shows a steady-state exposure of 13.3% relative to linagliptin.

Excretion

Following administration of an oral [^14C]-linagliptin dose to healthy subjects, approximately 85% of the administered radioactivity was eliminated via the enterohepatic system (80%) or urine (5%) within 4 days of dosing.

Specific Populations

Patients with Renal Impairment

An open-label pharmacokinetic study evaluated the pharmacokinetics of linagliptin 5 mg in male and female patients with varying degrees of chronic renal impairment. The study included 6 healthy subjects with normal renal function (creatinine clearance [CrCl] ≥80 mL/min), 6 patients with mild renal impairment (CrCl 50 to <80 mL/min), 6 patients with moderate renal impairment (CrCl 30 to <50 mL/min), 10 patients with type 2 diabetes mellitus and severe renal impairment (CrCl <30 mL/min), and 11 patients with type 2 diabetes mellitus and normal renal function. Creatinine clearance was measured by 24-hour urinary creatinine clearance measurements or estimated from serum creatinine based on the Cockcroft-Gault formula.

Under steady-state conditions, linagliptin exposure in patients with mild renal impairment was comparable to healthy subjects.

In patients with moderate renal impairment under steady-state conditions, mean exposure of linagliptin increased (AUCτ,ss by 71% and Cmax by 46%) compared with healthy subjects. This increase was not associated with a prolonged accumulation half-life, terminal half-life, or an increased accumulation factor. Renal excretion of linagliptin was below 5% of the administered dose and was not affected by decreased renal function.

Patients with type 2 diabetes mellitus and severe renal impairment showed steady-state exposure approximately 40% higher than that of patients with type 2 diabetes mellitus and normal renal function (increase in AUCτ,ss by 42% and Cmax by 35%). For both type 2 diabetes mellitus groups, renal excretion was below 7% of the administered dose.

These findings were further supported by the results of population pharmacokinetic analyses.

Patients with Hepatic Impairment

In patients with mild hepatic impairment (Child-Pugh class A), steady-state exposure (AUCτ,ss) of linagliptin was approximately 25% lower and Cmax,ss was approximately 36% lower than in healthy subjects. In patients with moderate hepatic impairment (Child-Pugh class B), AUCss of linagliptin was about 14% lower and Cmax,ss was approximately 8% lower than in healthy subjects. Patients with severe hepatic impairment (Child-Pugh class C) had comparable exposure of linagliptin in terms of AUC0-24 and approximately 23% lower Cmax compared with healthy subjects. Reductions in the pharmacokinetic parameters seen in patients with hepatic impairment did not result in reductions in DPP-4 inhibition.

Effects of Age, Body Mass Index (BMI), Gender, and Race

Based on the population pharmacokinetic analysis, age, BMI, gender, and race do not have a clinically meaningful effect on the pharmacokinetics of linagliptin [see Use in Specific Populations (8.5)].

Drug Interaction Studies

In vitro Assessment of Drug Interactions

Linagliptin is a weak to moderate inhibitor of CYP isozyme CYP3A4, but does not inhibit other CYP isozymes and is not an inducer of CYP isozymes, including CYP1A2, 2A6, 2B6, 2C8, 2C9, 2C19, 2D6, 2E1, and 4A11.

Linagliptin is a P-glycoprotein (P-gp) substrate, and inhibits P-gp mediated transport of digoxin at high concentrations. Based on these results and in vivo drug interaction studies, linagliptin is considered unlikely to cause interactions with other P-gp substrates at therapeutic concentrations.

In vivo Assessment of Drug Interactions

Strong inducers of CYP3A4 or P-gp (e.g., rifampin) decrease exposure to linagliptin to subtherapeutic and likely ineffective concentrations [see Drug Interactions (7)]. In vivo studies indicated evidence of a low propensity for causing drug interactions with substrates of CYP3A4, CYP2C9, CYP2C8, P-gp and organic cationic transporter (OCT).

Table 3 describes the effect of coadministered drugs on systemic exposure of linagliptin.

Table 3 Effect of Coadministered Drugs on Systemic Exposure of Linagliptin
Coadministered Drug | Dosing of Coadministered Drug* | Dosing of Linagliptin* | Geometric Mean Ratio (ratio with/without coadministered drug) No effect = 1.0
Coadministered Drug | Dosing of Coadministered Drug* | Dosing of Linagliptin* | AUC† | Cmax
Metformin | 850 mg TID | 10 mg QD | 1.20 | 1.03
Glyburide | 1.75 mg# | 5 mg QD | 1.02 | 1.01
Pioglitazone | 45 mg QD | 10 mg QD | 1.13 | 1.07
Ritonavir | 200 mg BID | 5 mg# | 2.01 | 2.96
Rifampin** | 600 mg QD | 5 mg QD | 0.60 | 0.56
*Multiple dose (steady-state) unless otherwise noted
**For information regarding clinical recommendations [see Drug Interactions (7.1)].
#Single dose
†AUC = AUC(0 to 24 hours) for single-dose treatments and AUC = AUC(TAU) for multiple-dose treatments
QD = once daily
BID = twice daily
TID = three times daily

Table 4 describes the effect of linagliptin on systemic exposure of coadministered drugs.

Table 4 Effect of Linagliptin on Systemic Exposure of Coadministered Drugs
Coadministered Drug | Dosing of Coadministered Drug* | Dosing of Linagliptin* | Geometric Mean Ratio (ratio with/without coadministered drug) No effect = 1.0
Coadministered Drug | Dosing of Coadministered Drug* | Dosing of Linagliptin* |  | AUC† | Cmax
Metformin | 850 mg TID | 10 mg QD | metformin | 1.01 | 0.89
Glyburide | 1.75 mg# | 5 mg QD | glyburide | 0.86 | 0.86
Pioglitazone | 45 mg QD | 10 mg QD | pioglitazone metabolite M-III metabolite M-IV | 0.94 0.98 1.04 | 0.86 0.96 1.05
Digoxin | 0.25 mg QD | 5 mg QD | digoxin | 1.02 | 0.94
Simvastatin | 40 mg QD | 10 mg QD | simvastatin simvastatin acid | 1.34 1.33 | 1.10 1.21
Warfarin | 10 mg# | 5 mg QD | R-warfarin S-warfarin INR PT | 0.99 1.03 0.93** 1.03** | 1.00 1.01 1.04** 1.15**
Ethinylestradiol and levonorgestrel | ethinylestradiol 0.03 mg and levonorgestrel 0.150 mg QD | 5 mg QD | ethinylestradiol levonorgestrel | 1.01 1.09 | 1.08 1.13
*Multiple dose (steady-state) unless otherwise noted
#Single dose
†AUC=AUC(INF) for single-dose treatments and AUC = AUC(TAU) for multiple-dose treatments
**AUC=AUC(0-168) and Cmax=Emax for pharmacodynamic end points
INR = International Normalized Ratio
PT = Prothrombin Time
QD = once daily
TID = three times daily

13 NONCLINICAL TOXICOLOGY

13.1 Carcinogenesis, Mutagenesis, Impairment of Fertility

Linagliptin did not increase the incidence of tumors in male and female rats in a 2-year study at doses of 6, 18, and 60 mg/kg. The highest dose of 60 mg/kg is approximately 418 times the clinical dose of 5 mg/day based on AUC exposure. Linagliptin did not increase the incidence of tumors in mice in a 2-year study at doses up to 80 mg/kg (males) and 25 mg/kg (females), or approximately 35- and 270-times the clinical dose based on AUC exposure. Higher doses of linagliptin in female mice (80 mg/kg) increased the incidence of lymphoma at approximately 215-times the clinical dose based on AUC exposure.

Linagliptin was not mutagenic or clastogenic with or without metabolic activation in the Ames bacterial mutagenicity assay, a chromosomal aberration test in human lymphocytes, and an in vivo micronucleus assay.

In fertility studies in rats, linagliptin had no adverse effects on early embryonic development, mating, fertility, or bearing live young up to the highest dose of 240 mg/kg (approximately 943-times the clinical dose based on AUC exposure).

14 CLINICAL STUDIES

14.1 Glycemic Control Trials in Adults with Type 2 Diabetes Mellitus

TRADJENTA has been studied as monotherapy and in combination with metformin, sulfonylurea, pioglitazone, and insulin. TRADJENTA has also been studied in patients with type 2 diabetes mellitus and severe chronic renal impairment.

In patients with type 2 diabetes mellitus, treatment with TRADJENTA produced clinically significant improvements in hemoglobin A1c (A1C), fasting plasma glucose (FPG), and 2-hour post-prandial glucose (PPG) compared with placebo.

Monotherapy

A total of 730 patients with type 2 diabetes mellitus participated in 2 double-blind, placebo-controlled studies, one of 18 weeks' and another of 24 weeks' duration, to evaluate the efficacy and safety of TRADJENTA monotherapy. In both monotherapy studies, patients currently on an antihyperglycemic agent discontinued the agent and underwent a diet, exercise, and drug washout period of about 6 weeks that included an open-label placebo run-in during the last 2 weeks. Patients with inadequate glycemic control (A1C 7% to 10%) after the washout period were randomized; patients not currently on antihyperglycemic agents (off therapy for at least 8 weeks) with inadequate glycemic control (A1C 7% to 10%) were randomized after completing the 2-week, open-label, placebo run-in period. In the 18-week trial, only patients ineligible for metformin were recruited. In the 18-week trial, 76 patients were randomized to placebo and 151 to TRADJENTA 5 mg; in the 24-week trial, 167 patients were randomized to placebo and 336 to TRADJENTA 5 mg. Patients who failed to meet specific glycemic goals during the 18-week trial received rescue therapy with pioglitazone and/or insulin; metformin rescue therapy was used in the 24-week trial.

Treatment with TRADJENTA 5 mg daily provided statistically significant improvements in A1C, FPG, and 2-hour PPG compared with placebo (Table 5). In the 18-week trial, 12% of patients receiving TRADJENTA 5 mg and 18% who received placebo required rescue therapy. In the 24-week trial, 10.2% of patients receiving TRADJENTA 5 mg and 20.9% of patients receiving placebo required rescue therapy. The improvement in A1C compared with placebo was not affected by gender, age, race, prior antihyperglycemic therapy, baseline BMI, or a standard index of insulin resistance (HOMA-IR). As is typical for trials of agents to treat type 2 diabetes mellitus, the mean reduction in A1C with TRADJENTA appears to be related to the degree of A1C elevation at baseline. In these 18- and 24-week studies, the changes from baseline in A1C were -0.4% and -0.4%, respectively, for those given TRADJENTA, and 0.1% and 0.3%, respectively, for those given placebo. Change from baseline in body weight did not differ significantly between the groups.

Table 5Glycemic Parameters in Placebo-Controlled Monotherapy Trials of TRADJENTA*
 | 18-Week Trial |  | 24-Week Trial
 | TRADJENTA 5 mg | Placebo | TRADJENTA 5 mg | Placebo
A1C (%)
Number of patients | n = 147 | n = 73 | n = 333 | n = 163
Baseline (mean) | 8.1 | 8.1 | 8.0 | 8.0
Change from baseline (adjusted mean***) | -0.4 | 0.1 | -0.4 | 0.3
Difference from placebo (adjusted mean) (95% CI) | -0.6 (-0.9, -0.3) | -- | -0.7 (-0.9, -0.5) | --
Patients [n (%)] achieving A1C <7%** | 32 (23.5) | 8 (11.8) | 77 (25) | 17 (12)
FPG (mg/dL)
Number of patients | n = 138 | n = 66 | n = 318 | n = 149
Baseline (mean) | 178 | 176 | 164 | 166
Change from baseline (adjusted mean***) | -13 | 7 | -9 | 15
Difference from placebo (adjusted mean) (95% CI) | -21 (-31, -10) | -- | -23 (-30, -16) | --
2-hour PPG (mg/dL)
Number of patients | Data not available | Data not available | n = 67 | n = 24
Baseline (mean) | -- | -- | 258 | 244
Change from baseline (adjusted mean***) | -- | -- | -34 | 25
Difference from placebo (adjusted mean) (95% CI) | -- | -- | -58 (-82, -34) | --
*Full analysis population using last observation on trial
**18-week trial: Placebo, n=68; TRADJENTA, n=136
24-week trial: Placebo, n=147; TRADJENTA, n=306
***18-week trial. HbA1c: ANCOVA model included treatment, reason for metformin intolerance and number of prior oral anti-diabetic medicine(s) (OADs) as class-effects, as well as baseline HbA1c as continuous covariates. FPG: ANCOVA model included treatment, reason for metformin intolerance and number of prior OADs as class-effects, as well as baseline HbA1c and baseline FPG as continuous covariates.
24-week trial. HbA1c: ANCOVA model included treatment and number of prior OADs as class-effects, as well as baseline HbA1c as continuous covariates. FPG: ANCOVA model included treatment and number of prior OADs as class-effects, as well as baseline HbA1c and baseline FPG as continuous covariates. PPG: ANCOVA model included treatment and number of prior OADs as class-effects, as well as baseline HbA1c and baseline postprandial glucose after two hours as covariate.

Add-on Combination Therapy with Metformin

A total of 701 patients with type 2 diabetes mellitus participated in a 24-week, randomized, double-blind, placebo-controlled trial designed to assess the efficacy of TRADJENTA in combination with metformin. Patients already on metformin (n = 491) at a dosage of at least 1,500 mg per day were randomized after completing a 2-week, open-label, placebo run-in period. Patients on metformin and another antihyperglycemic agent (n = 207) were randomized after a run-in period of approximately 6 weeks on metformin (at a dosage of at least 1,500 mg per day) in monotherapy. Patients were randomized to the addition of either TRADJENTA 5 mg or placebo, administered once daily. Patients who failed to meet specific glycemic goals during the studies were treated with glimepiride rescue.

In combination with metformin, TRADJENTA provided statistically significant improvements in A1C, FPG, and 2-hour PPG compared with placebo (Table 6). Rescue glycemic therapy was used in 7.8% of patients treated with TRADJENTA 5 mg and in 18.9% of patients treated with placebo. A similar decrease in body weight was observed for both treatment groups.

Table 6Glycemic Parameters in Placebo-Controlled Trial for TRADJENTA in Combination with Metformin*
 | TRADJENTA 5 mg + Metformin | Placebo + Metformin
A1C (%)
Number of patients | n = 513 | n = 175
Baseline (mean) | 8.1 | 8.0
Change from baseline (adjusted mean***) | -0.5 | 0.15
Difference from placebo + metformin (adjusted mean) (95% CI) | -0.6 (-0.8, -0.5) | --
Patients [n (%)] achieving A1C <7%** | 127 (26.2) | 15 (9.2)
FPG (mg/dL)
Number of patients | n = 495 | n = 159
Baseline (mean) | 169 | 164
Change from baseline (adjusted mean***) | -11 | 11
Difference from placebo + metformin (adjusted mean) (95% CI) | -21 (-27, -15) | --
2-hour PPG (mg/dL)
Number of patients | n = 78 | n = 21
Baseline (mean) | 270 | 274
Change from baseline (adjusted mean***) | -49 | 18
Difference from placebo + metformin (adjusted mean) (95% CI) | -67 (-95, -40) | --
*Full analysis population using last observation on trial
**TRADJENTA 5 mg + Metformin, n=485; Placebo + Metformin, n=163
***HbA1c: ANCOVA model included treatment and number of prior oral OADs as class-effects, as well as baseline HbA1c as continuous covariates. FPG: ANCOVA model included treatment and number of prior OADs as class-effects, as well as baseline HbA1c and baseline FPG as continuous covariates. PPG: ANCOVA model included treatment and number of prior OADs as class-effects, as well as baseline HbA1c and baseline postprandial glucose after two hours as covariate.

Initial Combination Therapy with Metformin

A total of 791 patients with type 2 diabetes mellitus and inadequate glycemic control on diet and exercise participated in the 24-week, randomized, double-blind, portion of this placebo-controlled factorial trial designed to assess the efficacy of TRADJENTA as initial therapy with metformin. Patients on an antihyperglycemic agent (52%) underwent a drug washout period of 4 weeks' duration. After the washout period and after completing a 2-week single-blind placebo run-in period, patients with inadequate glycemic control (A1C ≥7.0% to ≤10.5%) were randomized. Patients with inadequate glycemic control (A1C ≥7.5% to <11.0%) not on antihyperglycemic agents at trial entry (48%) immediately entered the 2-week, single-blind, placebo run-in period and then were randomized. Randomization was stratified by baseline A1C (<8.5% vs ≥8.5%) and use of a prior oral antidiabetic drug (none vs monotherapy). Patients were randomized in a 1:2:2:2:2:2 ratio to either placebo or one of 5 active-treatment arms. Approximately equal numbers of patients were randomized to receive initial therapy with 5 mg of TRADJENTA once daily, 500 mg or 1,000 mg of metformin twice daily, or 2.5 mg of linagliptin twice daily in combination with 500 mg or 1,000 mg of metformin twice daily. Patients who failed to meet specific glycemic goals during the trial were treated with sulfonylurea, thiazolidinedione, or insulin rescue therapy.

Initial therapy with the combination of linagliptin and metformin provided significant improvements in A1C and fasting plasma glucose (FPG) compared to placebo, to metformin alone, and to linagliptin alone (Table 7).

The adjusted mean treatment difference in A1C from baseline to week 24 (LOCF) was -0.5% (95% CI -0.7, -0.3; p<0.0001) for linagliptin 2.5 mg/metformin 1,000 mg twice daily compared to metformin 1,000 twice daily; -1.1% (95% CI -1.4, -0.9; p<0.0001) for linagliptin 2.5 mg/metformin 1,000 mg twice daily compared to TRADJENTA 5 mg once daily; -0.6% (95% CI -0.8, -0.4; p<0.0001) for linagliptin 2.5 mg/metformin 500 mg twice daily compared to metformin 500 mg twice daily; and -0.8% (95% CI -1.0, -0.6; p<0.0001) for linagliptin 2.5 mg/metformin 500 mg twice daily compared to TRADJENTA 5 mg once daily.

Lipid effects were generally neutral. No meaningful change in body weight was noted in any of the 6 treatment groups.

Table 7Glycemic Parameters at Final Visit (24-Week Trial) for Linagliptin and Metformin, Alone and in Combination in Randomized Patients with Type 2 Diabetes Mellitus Inadequately Controlled on Diet and Exercise**
 | Placebo | TRADJENTA 5 mg Once Daily* | Metformin 500 mg Twice Daily | Linagliptin 2.5 mg Twice Daily* + Metformin 500 mg Twice Daily | Metformin 1,000 mg Twice Daily | Linagliptin 2.5 mg Twice Daily* + Metformin 1,000 mg Twice Daily
A1C (%)
Number of patients | n = 65 | n = 135 | n = 141 | n = 137 | n = 138 | n = 140
Baseline (mean) | 8.7 | 8.7 | 8.7 | 8.7 | 8.5 | 8.7
Change from baseline (adjusted mean****) | 0.1 | -0.5 | -0.6 | -1.2 | -1.1 | -1.6
Difference from placebo (adjusted mean) (95% CI) | -- | -0.6 (-0.9, -0.3) | -0.8 (-1.0, -0.5) | -1.3 (-1.6, -1.1) | -1.2 (-1.5, -0.9) | -1.7 (-2.0, -1.4)
Patients [n (%)] achieving A1C <7%*** | 7 (10.8) | 14 (10.4) | 26 (18.6) | 41 (30.1) | 42 (30.7) | 74 (53.6)
Patients (%) receiving rescue medication | 29.2 | 11.1 | 13.5 | 7.3 | 8.0 | 4.3
FPG (mg/dL)
Number of patients | n = 61 | n = 134 | n = 136 | n = 135 | n = 132 | n = 136
Baseline (mean) | 203 | 195 | 191 | 199 | 191 | 196
Change from baseline (adjusted mean****) | 10 | -9 | -16 | -33 | -32 | -49
Difference from placebo (adjusted mean) (95% CI) | -- | -19 (-31, -6) | -26 (-38, -14) | -43 (-56, -31) | -42 (-55, -30) | -60 (-72, -47)
*Total daily dosage of TRADJENTA is equal to 5 mg
**Full analysis population using last observation on trial
***Metformin 500 mg twice daily, n=140; Linagliptin 2.5 mg twice daily + Metformin 500 twice daily, n=136; Metformin 1,000 mg twice daily, n=137; Linagliptin 2.5 mg twice daily + Metformin 1,000 mg twice daily, n=138
****HbA1c: ANCOVA model included treatment and number of prior OADs as class-effects, as well as baseline HbA1c as continuous covariates. FPG: ANCOVA model included treatment and number of prior OADs as class-effects, as well as baseline HbA1c and baseline FPG as continuous covariates.

Active-Controlled Trial vs Glimepiride in Combination with Metformin

The efficacy of TRADJENTA was evaluated in a 104-week, double-blind, glimepiride-controlled, non-inferiority trial in patients with type 2 diabetes mellitus with insufficient glycemic control despite metformin therapy. Patients being treated with metformin only entered a run-in period of 2 weeks' duration, whereas patients pretreated with metformin and one additional antihyperglycemic agent entered a run-in treatment period of 6 weeks' duration with metformin monotherapy (dosage of ≥1,500 mg/day) and washout of the other agent. After an additional 2-week placebo run-in period, those with inadequate glycemic control (A1C 6.5% to 10%) were randomized 1:1 to the addition of TRADJENTA 5 mg once daily or glimepiride. Randomization was stratified by baseline HbA1c (<8.5% vs ≥8.5%), and the previous use of antidiabetic drugs (metformin alone vs metformin plus one other OAD). Patients receiving glimepiride were given an initial dosage of 1 mg/day and then electively titrated over the next 12 weeks to a maximum dosage of 4 mg/day as needed to optimize glycemic control. Thereafter, the glimepiride dosage was to be kept constant, except for down-titration to prevent hypoglycemia.

After 52 and 104 weeks, TRADJENTA and glimepiride both had reductions from baseline in A1C (52 weeks: -0.4% for TRADJENTA, -0.6% for glimepiride; 104 weeks: -0.2% for TRADJENTA, -0.4% for glimepiride) from a baseline mean of 7.7% (Table 8). The mean difference between groups in A1C change from baseline was 0.2% with 2-sided 97.5% confidence interval (0.1%, 0.3%) for the intent-to-treat population using last observation carried forward. These results were consistent with the completers analysis.

Table 8Glycemic Parameters at 52 and 104 Weeks in Trial Comparing TRADJENTA to Glimepiride as Add-On Therapy in Patients Inadequately Controlled on Metformin**
 | Week 52 |  | Week 104
 | TRADJENTA 5 mg + Metformin | Glimepiride + Metformin (mean Glimepiride dosage 3 mg) | TRADJENTA 5 mg + Metformin | Glimepiride + Metformin (mean Glimepiride dosage 3 mg)
A1C (%)
Number of patients | n = 764 | n = 755 | n = 764 | n = 755
Baseline (mean) | 7.7 | 7.7 | 7.7 | 7.7
Change from baseline (adjusted mean****) | -0.4 | -0.6 | -0.2 | -0.4
Difference from glimepiride (adjusted mean) (97.5% CI) | 0.2 (0.1, 0.3) | -- | 0.2 (0.1, 0.3) | --
FPG (mg/dL)
Number of patients | n = 733 | n = 725 | n = 733 | n = 725
Baseline (mean) | 164 | 166 | 164 | 166
Change from baseline (adjusted mean****) | -8* | -15 | -2† | -9
Hypoglycemia incidence (%)***
Number of patients | n = 776 | n = 775 | n = 776 | n = 775
Incidence**** | 5.3* | 31.1 | 7.5* | 36.1
*p<0.0001 vs glimepiride; †p=0.0012 vs glimepiride
**Full analysis population using last observation on trial
***Hypoglycemic incidence included both asymptomatic events (not accompanied by typical symptoms and plasma glucose concentration of ≤70 mg/dL) and symptomatic events with typical symptoms of hypoglycemia and plasma glucose concentration of ≤70 mg/dL.
****HbA1c: ANCOVA model included treatment and number of prior OADs as class-effects, as well as baseline HbA1c as continuous covariates. FPG: ANCOVA model included treatment and number of prior OADs as class-effects, as well as baseline HbA1c and baseline FPG as continuous covariates. Hypoglycemia incidence (%): Cochran-Mantel-Haenszel test was performed on the patient population contained in the treated set, to compare the proportion of patients with hypoglycemic events between patients treated with linagliptin and patients treated with glimepiride.

Patients treated with linagliptin had a mean baseline body weight of 86 kg and were observed to have an adjusted mean decrease in body weight of 1.1 kg at 52 weeks and 1.4 kg at 104 weeks. Patients on glimepiride had a mean baseline body weight of 87 kg and were observed to have an adjusted mean increase from baseline in body weight of 1.4 kg at 52 weeks and 1.3 kg at 104 weeks (treatment difference p<0.0001 for both timepoints).

Add-On Combination Therapy with Pioglitazone

A total of 389 patients with type 2 diabetes mellitus participated in a 24-week, randomized, double-blind, placebo-controlled trial designed to assess the efficacy of TRADJENTA in combination with pioglitazone. Therapy was stopped in patients on oral antihyperglycemic therapy for a period of 6 weeks (4 weeks followed by a 2-week, open-label, placebo run-in period). Drug-naïve patients entered directly into the 2-week placebo run-in period. After the run-in period, patients were randomized to receive either TRADJENTA 5 mg or placebo, both in addition to pioglitazone 30 mg daily. Patients who failed to meet specific glycemic goals during the studies were treated with metformin rescue. Glycemic endpoints measured were A1C and FPG.

In initial combination with pioglitazone 30 mg, TRADJENTA 5 mg provided statistically significant improvements in A1C and FPG compared to placebo with pioglitazone (Table 9). Rescue therapy was used in 7.9% of patients treated with TRADJENTA 5 mg/pioglitazone 30 mg and 14.1% of patients treated with placebo/pioglitazone 30 mg. Patient weight increased in both groups during the trial with an adjusted mean change from baseline of 2.3 kg and 1.2 kg in the TRADJENTA 5 mg/pioglitazone 30 mg and placebo/pioglitazone 30 mg groups, respectively (p = 0.0141).

Table 9Glycemic Parameters in Placebo-Controlled Trial for TRADJENTA in Combination Therapy with Pioglitazone*
 | TRADJENTA 5 mg + Pioglitazone | Placebo + Pioglitazone
A1C (%)
Number of patients | n = 252 | n = 128
Baseline (mean) | 8.6 | 8.6
Change from baseline (adjusted mean**) | -1.1 | -0.6
Difference from placebo + pioglitazone (adjusted mean) (95% CI) | -0.5 (-0.7, -0.3) | --
Patients [n (%)] achieving A1C <7% | 108 (42.9) | 39 (30.5)
FPG (mg/dL)
Number of patients | n = 243 | n = 122
Baseline (mean) | 188 | 186
Change from baseline (adjusted mean**) | -33 | -18
Difference from placebo + pioglitazone (adjusted mean) (95% CI) | -14 (-21, -7) | --
*Full analysis population using last observation on trial
**HbA1c: ANCOVA model included treatment and number of prior OADs as class-effects, as well as baseline HbA1c as continuous covariates. FPG: ANCOVA model included treatment and number of prior OADs as class-effects, as well as baseline HbA1c and baseline FPG as continuous covariates.

Add-On Combination with Sulfonylureas

A total of 245 patients with type 2 diabetes mellitus participated in an 18-week, randomized, double-blind, placebo-controlled trial designed to assess the efficacy of TRADJENTA in combination with sulfonylurea (SU). Patients on sulfonylurea monotherapy (n = 142) were randomized after completing a 2-week, single-blind, placebo run-in period. Patients on a sulfonylurea plus one additional oral antihyperglycemic agent (n = 103) were randomized after a wash-out period of 4 weeks and a 2-week, single-blind, placebo run-in period. Patients were randomized to the addition of TRADJENTA 5 mg or to placebo, each administered once daily. Patients who failed to meet specific glycemic goals during the studies were treated with metformin rescue. Glycemic endpoints measured included A1C and FPG.

In combination with a sulfonylurea, TRADJENTA provided statistically significant improvements in A1C compared with placebo following 18 weeks' treatment; the improvements in FPG observed with TRADJENTA were not statistically significant compared with placebo (Table 10). Rescue therapy was used in 7.6% of patients treated with TRADJENTA 5 mg and 15.9% of patients treated with placebo. There was no significant difference between TRADJENTA and placebo in body weight.

Table 10Glycemic Parameters in Placebo-Controlled Trial for TRADJENTA in Combination with Sulfonylurea*
 | TRADJENTA 5 mg + SU | Placebo + SU
A1C (%)
Number of patients | n = 158 | n = 82
Baseline (mean) | 8.6 | 8.6
Change from baseline (adjusted mean***) | -0.5 | -0.1
Difference from placebo + SU (adjusted mean) (95% CI) | -0.5 (-0.7, -0.2) | --
Patients [n (%)] achieving A1C <7%** | 23 (14.7) | 3 (3.7)
FPG (mg/dL)
Number of patients | n = 155 | n = 78
Baseline (mean) | 180 | 171
Change from baseline (adjusted mean***) | -8 | -2
Difference from placebo + SU (adjusted mean) (95% CI) | -6 (-17, 4) | --
SU = sulfonylurea
*Full analysis population using last observation on trial
**TRADJENTA 5 mg + SU, n=156; Placebo + SU, n=82
***HbA1c: ANCOVA model included treatment and number of prior OADs as class-effects, as well as baseline HbA1c as continuous covariates. FPG: ANCOVA model included treatment and number of prior OADs as class-effects, as well as baseline HbA1c and baseline FPG as continuous covariates

Add-On Combination Therapy with Metformin and a Sulfonylurea

A total of 1,058 patients with type 2 diabetes mellitus participated in a 24-week, randomized, double-blind, placebo-controlled trial designed to assess the efficacy of TRADJENTA in combination with a sulfonylurea and metformin. The most common sulfonylureas used by patients in the trial were: glimepiride (31%), glibenclamide (26%), and gliclazide (26%, not available in the United States). Patients on a sulfonylurea and metformin were randomized to receive TRADJENTA 5 mg or placebo, each administered once daily. Patients who failed to meet specific glycemic goals during the trial were treated with pioglitazone rescue. Glycemic endpoints measured included A1C and FPG.

In combination with a sulfonylurea and metformin, TRADJENTA provided statistically significant improvements in A1C and FPG compared with placebo (Table 11). In the entire trial population (patients on TRADJENTA in combination with sulfonylurea and metformin), a mean reduction from baseline relative to placebo in A1C of -0.6% and in FPG of -13 mg/dL was seen. Rescue therapy was used in 5.4% of patients treated with TRADJENTA 5 mg and in 13% of patients treated with placebo. Change from baseline in body weight did not differ significantly between the groups.

Table 11Glycemic Parameters in Placebo-Controlled Trial for TRADJENTA in Combination with Metformin and Sulfonylurea*
 | TRADJENTA 5 mg + Metformin + SU | Placebo + Metformin + SU
A1C (%)
Number of patients | n = 778 | n = 262
Baseline (mean) | 8.2 | 8.1
Change from baseline (adjusted mean***) | -0.7 | -0.1
Difference from placebo (adjusted mean) (95% CI) | -0.6 (-0.7, -0.5) | --
Patients [n (%)] achieving A1C <7%** | 217 (29.2) | 20 (8.1)
FPG (mg/dL)
Number of patients | n = 739 | n = 248
Baseline (mean) | 159 | 163
Change from baseline (adjusted mean***) | -5 | 8
Difference from placebo (adjusted mean) (95% CI) | -13 (-18, -7) | --
SU = sulfonylurea
*Full analysis population using last observation on trial
**TRADJENTA 5 mg + Metformin + SU, n=742; Placebo + Metformin + SU, n=247
***HbA1c: ANCOVA model included treatment as class-effects and baseline HbA1c as continuous covariates. FPG: ANCOVA model included treatment as class-effects, as well as baseline HbA1c and baseline FPG as continuous covariates.

Add-On Combination Therapy with Insulin

A total of 1,261 patients with type 2 diabetes mellitus inadequately controlled on basal insulin alone or basal insulin in combination with oral drugs participated in a randomized, double-blind, placebo-controlled trial designed to evaluate the efficacy of TRADJENTA as add-on therapy to basal insulin over 24 weeks. Randomization was stratified by baseline HbA1c (<8.5% vs ≥8.5%), renal function impairment status (based on baseline eGFR), and concomitant use of oral antidiabetic drugs (none, metformin only, pioglitazone only, metformin + pioglitazone). Patients with a baseline A1C of ≥7% and ≤10% were included in the trial including 709 patients with renal impairment (eGFR <90 mL/min), most of whom (n=575) were categorized as mild renal impairment (eGFR 60 to <90 mL/min). Patients entered a 2 week placebo run-in period on basal insulin (e.g., insulin glargine, insulin detemir, or NPH insulin) with or without metformin and/or pioglitazone background therapy. Following the run-in period, patients with inadequate glycemic control were randomized to the addition of either 5 mg of TRADJENTA or placebo, administered once daily. Patients were maintained on a stable dosage of insulin prior to enrollment, during the run-in period, and during the first 24 weeks of treatment. Patients who failed to meet specific glycemic goals during the double-blind treatment period were rescued by increasing background insulin dosage.

TRADJENTA used in combination with insulin (with or without metformin and/or pioglitazone), provided statistically significant improvements in A1C and FPG compared to placebo (Table 12) after 24 weeks of treatment. The mean total daily insulin dosage at baseline was 42 units for patients treated with TRADJENTA and 40 units for patients treated with placebo. Background baseline diabetes mellitus therapy included use of: insulin alone (16.1%), insulin combined with metformin only (75.5%), insulin combined with metformin and pioglitazone (7.4%), and insulin combined with pioglitazone only (1%). The mean change from baseline to Week 24 in the daily dosage of insulin was +1.3 IU in the placebo group and +0.6 IU in the TRADJENTA group. The mean change in body weight from baseline to Week 24 was similar in the two treatment groups.

Table 12Glycemic Parameters in Placebo-Controlled Trial for TRADJENTA in Combination with Insulin*
 | TRADJENTA 5 mg + Insulin | Placebo + Insulin
A1C (%)
Number of patients | n = 618 | n = 617
Baseline (mean) | 8.3 | 8.3
Change from baseline (adjusted mean***) | -0.6 | 0.1
Difference from placebo (adjusted mean) (95% CI) | -0.7 (-0.7, -0.6) | --
Patients [n (%)] achieving A1C <7%** | 116 (19.5) | 48 (8.1)
FPG (mg/dL)
Number of patients | n = 613 | n = 608
Baseline (mean) | 147 | 151
Change from baseline (adjusted mean***) | -8 | 3
Difference from placebo (adjusted mean) (95% CI) | -11 (-16, -6) | --
*Full analysis population using last observation carried forward (LOCF) method on trial
**TRADJENTA + Insulin, n=595; Placebo + Insulin, n=593
***HbA1c: ANCOVA model included treatment, categorical renal function impairment status and concomitant OADs as class-effects, as well as baseline HbA1c as continuous covariates. FPG: ANCOVA model included treatment, categorical renal function impairment status and concomitant OADs as class-effects, as well as baseline HbA1c and baseline FPG as continuous covariates.

The difference between treatment with linagliptin and placebo in terms of adjusted mean change from baseline in HbA1c after 24 weeks was comparable for patients with no renal impairment (eGFR ≥90 mL/min, n=539), with mild renal impairment (eGFR 60 to <90 mL/min, n= 565), or with moderate renal impairment (eGFR 30 to <60 mL/min, n=124).

Renal Impairment

A total of 133 patients with type 2 diabetes mellitus participated in a 52 week, double-blind, randomized, placebo-controlled trial designed to evaluate the efficacy and safety of TRADJENTA in patients with both type 2 diabetes mellitus and severe chronic renal impairment. Participants with an estimated (based on the four variables modified diet in renal disease [MDRD] equation) GFR value of <30 mL/min were eligible to participate in the trial. Randomization was stratified by baseline HbA1c (≤8% and >8%) and background antidiabetic therapy (insulin or any combination with insulin, SU or glinides as monotherapy and pioglitazone or any other antidiabetics excluding any other DPP-4 inhibitors). For the initial 12 weeks of the trial, background antidiabetic therapy was kept stable and included insulin, sulfonylurea, glinides, and pioglitazone. For the remainder of the trial, dosage adjustments in antidiabetic background therapy were allowed. At baseline in this trial, 62.5% of patients were receiving insulin alone as background diabetes mellitus therapy, and 12.5% were receiving sulfonylurea alone.

After 12 weeks of treatment, TRADJENTA 5 mg provided statistically significant improvement in A1C compared to placebo, with an adjusted mean change of -0.6% compared to placebo (95% confidence interval -0.9, -0.3) based on the analysis using last observation carried forward (LOCF). With adjustments in antidiabetic background therapy after the initial 12 weeks, efficacy was maintained for 52 weeks, with an adjusted mean change from baseline in A1C of -0.7% compared to placebo (95% confidence interval -1.0, -0.4) based on analysis using LOCF.

14.2 Cardiovascular Safety Trials in Patients with Type 2 Diabetes Mellitus

CARMELINA

The cardiovascular risk of TRADJENTA was evaluated in CARMELINA, a multi-national, multi-center, placebo-controlled, double-blind, parallel group trial comparing TRADJENTA (N=3,494) to placebo (N=3,485) in adult patients with type 2 diabetes mellitus and a history of established macrovascular and/or renal disease. The trial compared the risk of major adverse cardiovascular events (MACE) between TRADJENTA and placebo when these were added to standard of care treatments for diabetes mellitus and other cardiovascular risk factors. The trial was event driven, the median duration of follow-up was 2.2 years and vital status was obtained for 99.7% of patients.

Patients were eligible to enter the trial if they were adults with type 2 diabetes mellitus, with HbA1c of 6.5% to 10%, and had either albuminuria and previous macrovascular disease (39% of enrolled population), or evidence of impaired renal function by eGFR and Urinary Albumin Creatinine Ratio (UACR) criteria (42% of enrolled population), or both (18% of enrolled population).

At baseline the mean age was 66 years and the population was 63% male, 80% White, 9% Asian, 6% Black or African American, and 36% were of Hispanic or Latino ethnicity. Mean HbA1c was 8.0% and mean duration of type 2 diabetes mellitus was 15 years. The trial population included 17% patients ≥75 years of age and 62% patients with renal impairment defined as eGFR <60 mL/min/1.73 m^2. The mean eGFR was 55 mL/min/1.73 m^2 and 27% of patients had mild renal impairment (eGFR 60 to 90 mL/min/1.73 m^2), 47% of patients had moderate renal impairment (eGFR 30 to <60 mL/min/1.73 m^2) and 15% of patients had severe renal impairment (eGFR <30 mL/min/1.73 m^2). Patients were taking at least one antidiabetic drug (97%), and the most common were insulin and analogues (57%), metformin (54%) and sulfonylurea (32%). Patients were also taking antihypertensives (96%), lipid lowering drugs (76%) with 72% on statin, and aspirin (62%).

The primary endpoint, MACE, was the time to first occurrence of one of three composite outcomes which included cardiovascular death, non-fatal myocardial infarction or non-fatal stroke. The trial was designed as a non-inferiority trial with a pre-specified risk margin of 1.3 for the hazard ratio of MACE.

The results of CARMELINA, including the contribution of each component to the primary composite endpoint, are shown in Table 13. The estimated hazard ratio for MACE associated with TRADJENTA relative to placebo was 1.02 with a 95% confidence interval of (0.89, 1.17). The upper bound of this confidence interval, 1.17, excluded the risk margin of 1.3. The Kaplan-Meier curve depicting time to first occurrence of MACE is shown in Figure 1.

Table 13Major Adverse Cardiovascular Events (MACE) by Treatment Group in the CARMELINA Trial
 | TRADJENTA 5 mg n = 3,494 |  | Placebo n = 3,485 |  | Hazard Ratio
 | Number of Subjects (%) | Incidence Rate per 1,000 PY* | Number of Subjects (%) | Incidence Rate per 1,000 PY* | (95% CI)
Composite of first event of CV death, non-fatal myocardial infarction (MI), or non-fatal stroke (MACE) | 434 (12.4) | 57.7 | 420 (12.1) | 56.3 | 1.02 (0.89, 1.17)
CV death** | 255 (7.3) | 32.6 | 264 (7.6) | 34.0 | 0.96 (0.81, 1.14)
Non-fatal MI** | 156 (4.5) | 20.6 | 135 (3.9) | 18.0 | 1.15 (0.91, 1.45)
Non-fatal stroke** | 65 (1.9) | 8.5 | 73 (2.1) | 9.6 | 0.88 (0.63, 1.23)
*PY=patient years
**A patient may have experienced more than one component; therefore, the sum of the components is larger than the number of patients who experienced the composite outcome.

Figure 1 Kaplan-Meier: Time to First Occurrence of MACE in the CARMELINA Trial

CAROLINA

The cardiovascular risk of TRADJENTA was evaluated in CAROLINA, a multi-center, multi-national, randomized, double-blind, parallel group trial comparing TRADJENTA (N=3,023) to glimepiride (N=3,010) in adult patients with type 2 diabetes mellitus and a history of established cardiovascular disease and/or multiple cardiovascular risk factors. The trial compared the risk of major adverse cardiovascular events (MACE) between TRADJENTA and glimepiride when these were added to standard of care treatments for diabetes mellitus and other cardiovascular risk factors. The trial was event driven, the median duration of follow-up was 6.23 years and vital status was obtained for 99.3% of patients.

Patients were eligible to enter the trial if they were adults with type 2 diabetes mellitus with insufficient glycemic control (defined as HbA1c of 6.5% to 8.5% or 6.5% to 7.5% depending on whether treatment-naïve, on monotherapy or on combination therapy), and were defined to be at high cardiovascular risk with previous vascular disease, evidence of vascular related end-organ damage, age ≥70 years, and/or two cardiovascular risk factors (duration of diabetes mellitus >10 years, systolic blood pressure >140 mmHg, current smoker, LDL cholesterol ≥135 mg/dL).

At baseline the mean age was 64 years and the population was 60% male, 73% White, 18% Asian, 5% Black or African American, and 17% were of Hispanic or Latino ethnicity. The mean HbA1c was 7.15% and mean duration of type 2 diabetes mellitus was 7.6 years. The trial population included 34% patients ≥70 years of age and 19% patients with renal impairment defined as eGFR <60 mL/min/1.73 m^2. The mean eGFR was 77 mL/min/1.73m^2. Patients were taking at least one antidiabetic drug (91%) and the most common were metformin (83%) and sulfonylurea (28%). Patients were also taking antihypertensives (89%), lipid lowering drugs (70%) with 65% on statin, and aspirin (47%).

The primary endpoint, MACE, was the time to first occurrence of one of three composite outcomes which included cardiovascular death, non-fatal myocardial infarction or non-fatal stroke. The trial was designed as a non-inferiority trial with a pre-specified risk margin of 1.3 for the upper bound of the 95% CI for the hazard ratio of MACE.

The results of CAROLINA, including the contribution of each component to the primary composite endpoint, are shown in Table 14. The Kaplan-Meier curve depicting time to first occurrence of MACE is shown in Figure 2.

Table 14Major Adverse Cardiovascular Events (MACE) by Treatment Group in the CAROLINA Trial
 | TRADJENTA 5 mg n=3,023 |  | Glimepiride (1 mg to 4 mg) n=3,010 |  | Hazard Ratio
 | Number of Subjects (%) | Incidence Rate per 1,000 PY* | Number of Subjects (%) | Incidence Rate per 1,000 PY* | (95% CI)
Composite of first event of CV death, non-fatal myocardial infarction (MI), or non-fatal stroke (MACE) | 356 (11.8) | 20.7 | 362 (12.0) | 21.2 | 0.98 (0.84, 1.14)
CV death** | 169 (5.6) | 9.2 | 168 (5.6) | 9.2 | 1.00 (0.81, 1.24)
Non-fatal MI** | 145 (4.8) | 8.3 | 142 (4.7) | 8.2 | 1.01 (0.80, 1.28)
Non-fatal stroke** | 91 (3.0) | 5.2 | 104 (3.5) | 6.0 | 0.87 (0.66, 1.15)
*PY=patient years
**A patient may have experienced more than one component; therefore, the sum of the components is larger than the number of patients who experienced the composite outcome

Figure 2 Time to First Occurrence of 3P-MACE in CAROLINA

16 HOW SUPPLIED/STORAGE AND HANDLING

TRADJENTA tablets are available as light red, round, biconvex, bevel-edged, film-coated tablets containing 5 mg of linagliptin. TRADJENTA tablets are debossed with "D5" on one side and the Boehringer Ingelheim symbol on the other side.

They are supplied as follows:

Bottles of approximately 2640 film-coated tablets, NDC 55154-0410-8

If repackaging is required, dispense in a tight container as defined in USP.

Storage

Store at 20°C to 25°C (68°F to 77°F); excursions permitted to 15°C to 30°C (59°F to 86°F) [see USP Controlled Room Temperature].

17 PATIENT COUNSELING INFORMATION

Advise the patient to read the FDA-approved patient labeling (Medication Guide).

Pancreatitis

Inform patients that acute pancreatitis has been reported during use of TRADJENTA. Inform patients that persistent severe abdominal pain, sometimes radiating to the back, which may or may not be accompanied by vomiting, is the hallmark symptom of acute pancreatitis. Instruct patients to discontinue TRADJENTA promptly and contact their healthcare provider if persistent severe abdominal pain occurs [see Warnings and Precautions (5.1)].

Hypoglycemia with Concomitant Use with Insulin and Insulin Secretagogues

Inform patients that the incidence of hypoglycemia is increased when TRADJENTA is used in combination with an insulin secretagogue (e.g., sulfonylurea) or insulin [see Warnings and Precautions (5.2)].

Hypersensitivity Reactions

Inform patients that serious allergic reactions, such as anaphylaxis, angioedema, and exfoliative skin conditions, have been reported during postmarketing use of TRADJENTA. If symptoms of allergic reactions (such as rash, skin flaking or peeling, urticaria, swelling of the skin, or swelling of the face, lips, tongue, and throat that may cause difficulty in breathing or swallowing) occur, patients must stop taking TRADJENTA and seek medical advice promptly [see Warnings and Precautions (5.3)].

Severe and Disabling Arthralgia

Inform patients that severe and disabling joint pain may occur with this class of drugs. The time to onset of symptoms can range from one day to years. Instruct patients to seek medical advice if severe joint pain occurs [see Warnings and Precautions (5.4)].

Bullous Pemphigoid

Inform patients that bullous pemphigoid has been reported during use of TRADJENTA. Instruct patients to seek medical advice if blisters or erosions occur [see Warnings and Precautions (5.5)].

Heart Failure

Inform patients of the signs and symptoms of heart failure. Before initiating TRADJENTA, patients should be asked about a history of heart failure or other risk factors for heart failure including moderate to severe renal impairment. Instruct patients to contact their healthcare provider as soon as possible if they experience symptoms of heart failure, including increasing shortness of breath, rapid increase in weight or swelling of the feet [see Warnings and Precautions (5.6)].

Missed Dose

Instruct patients to take TRADJENTA only as prescribed. If a dose is missed, it should be taken as soon as the patient remembers. Advise patients not to double their next dose.

Distributed by:
Boehringer Ingelheim Pharmaceuticals, Inc.
Ridgefield, CT 06877 USA

Licensed from:
Boehringer Ingelheim International GmbH, Ingelheim, Germany

TRADJENTA is a registered trademark of and used under license from Boehringer Ingelheim International GmbH.

Boehringer Ingelheim Pharmaceuticals, Inc. either owns or uses the CARMELINA® and CAROLINA® trademarks under license.

The other brands listed are trademarks of their respective owners and are not trademarks of Boehringer Ingelheim Pharmaceuticals, Inc.

Copyright © 2023 Boehringer Ingelheim International GmbH
ALL RIGHTS RESERVED

Distributed By:

Cardinal Health

Dublin, OH 43017

ER7866 Rev. C

COL10194BF212023
SPL10196B

MEDICATION GUIDE
TRADJENTA® (TRAD gen ta)
(linagliptin tablets)
for oral use

What is the most important information I should know about TRADJENTA?
TRADJENTA can cause serious side effects, including:

- Inflammation of the pancreas (pancreatitis) which may be severe and lead to death. Certain medical problems make you more likely to get pancreatitis.
  Before you start taking TRADJENTA, tell your healthcare provider if you have ever had:

- inflammation of your pancreas (pancreatitis)
- a history of alcoholism

- stones in your gallbladder (gallstones)
- high blood triglyceride levels

Stop taking TRADJENTA and call your healthcare provider right away if you have pain in your stomach area (abdomen) that is severe and will not go away. The pain may be felt going from your abdomen to your back. The pain may happen with or without vomiting. These may be symptoms of pancreatitis.

What is TRADJENTA?

- TRADJENTA is a prescription medicine used along with diet and exercise to lower blood sugar in adults with type 2 diabetes mellitus.
- TRADJENTA is not for people with type 1 diabetes mellitus.
- If you have had pancreatitis in the past, it is not known if you have a higher chance of getting pancreatitis while you take TRADJENTA.
- It is not known if TRADJENTA is safe and effective in children.

Who should not take TRADJENTA?
Do not take TRADJENTA if you:

- are allergic to linagliptin or any of the ingredients in TRADJENTA. See the end of this Medication Guide for a complete list of ingredients in TRADJENTA.
  Symptoms of a serious allergic reaction to TRADJENTA may include:
  - skin rash, itching, flaking or peeling
  - raised red patches on your skin (hives)
  - swelling of your face, lips, tongue and throat that may cause difficulty in breathing or swallowing
  - difficulty with swallowing or breathing

If you have any of these symptoms, stop taking TRADJENTA and call your healthcare provider right away or go to the nearest hospital emergency room.

What should I tell my healthcare provider before taking TRADJENTA?
Before taking TRADJENTA, tell your healthcare provider about all of your medical conditions, including if you:

- have or have had inflammation of your pancreas (pancreatitis).
- are pregnant or plan to become pregnant. It is not known if TRADJENTA will harm your unborn baby. If you are pregnant, talk with your healthcare provider about the best way to control your blood sugar while you are pregnant.
- are breastfeeding or plan to breastfeed. It is not known if TRADJENTA passes into your breast milk. Talk with your healthcare provider about the best way to feed your baby if you take TRADJENTA.

Tell your healthcare provider about all the medicines you take, including prescription and over-the-counter medicines, vitamins, and herbal supplements.
TRADJENTA may affect the way other medicines work, and other medicines may affect how TRADJENTA works.
Know the medicines you take. Keep a list of them to show your healthcare provider and pharmacist when you get a new medicine.

How should I take TRADJENTA?

- Take TRADJENTA exactly as your healthcare provider tells you to take it.
- Take 1 tablet 1 time each day with or without food.
- If you miss a dose, take it as soon as you remember. If you do not remember until it is time for your next dose, skip the missed dose and go back to your regular schedule. Do not take two doses of TRADJENTA at the same time.
- Your healthcare provider may tell you to take TRADJENTA along with other diabetes medicines. Low blood sugar can happen more often when TRADJENTA is taken with certain other diabetes medicines. See "What are the possible side effects of TRADJENTA?"
  If you take too much TRADJENTA, call your healthcare provider or local poison control center or go to the nearest hospital emergency room right away.

What are the possible side effects of TRADJENTA?
TRADJENTA may cause serious side effects, including:

- See "What is the most important information I should know about TRADJENTA?"
- Low blood sugar (hypoglycemia). If you take TRADJENTA with another medicine that can cause low blood sugar, such as a sulfonylurea or insulin, your risk of getting low blood sugar is higher. The dose of your sulfonylurea medicine or insulin may need to be lowered while you take TRADJENTA. Signs and symptoms of low blood sugar may include:

- headache
- irritability

- drowsiness
- hunger

- weakness
- fast heartbeat

- dizziness
- sweating

- confusion
- shaking or feeling jittery

- Allergic (hypersensitivity) reactions. Serious allergic reactions have happened in people who are taking TRADJENTA. Symptoms may include:

- swelling of your face, lips, tongue, throat, and other areas on your skin
- raised, red areas on your skin (hives)

- difficulty with swallowing or breathing
- skin rash, itching, flaking, or peeling

If you have any of these symptoms, stop taking TRADJENTA and call your healthcare provider right away or go to the nearest hospital emergency room.
1. Joint pain. Some people who take TRADJENTA, may develop joint pain that can be severe. Call your healthcare provider if you have severe joint pain.
2. Skin reaction. Some people who take medicines called DPP-4 inhibitors like TRADJENTA, may develop a skin reaction called bullous pemphigoid that can require treatment in a hospital. Tell your healthcare provider right away if you develop blisters or the breakdown of the outer layer of your skin (erosion). Your healthcare provider may tell you to stop taking TRADJENTA.
3. Heart failure. Heart failure means your heart does not pump blood well enough.
  Before you start taking TRADJENTA, tell your healthcare provider if you have ever had heart failure or have problems with your kidneys. Contact your healthcare provider right away if you have any of the following symptoms: These may be symptoms of heart failure.
  1. increasing shortness of breath or trouble breathing, especially when you lie down
  2. swelling or fluid retention, especially in the feet, ankles or legs
  3. an unusually fast increase in weight
  4. unusual tiredness

The most common side effects of TRADJENTA include:

- stuffy or runny nose and sore throat
- cough
- diarrhea
Tell your healthcare provider if you have any side effect that bothers you or that does not go away.
  These are not all the possible side effects of TRADJENTA. For more information, ask your healthcare provider or pharmacist.
  Call your doctor for medical advice about side effects. You may report side effects to FDA at 1-800-FDA-1088.

How should I store TRADJENTA?

- Store TRADJENTA at room temperature between 68°F and 77°F (20°C and 25°C).
- Keep TRADJENTA and all medicines out of the reach of children.

General information about the safe and effective use of TRADJENTA.
Medicines are sometimes prescribed for purposes other than those listed in a Medication Guide. Do not use TRADJENTA for a condition for which it was not prescribed. Do not give TRADJENTA to other people, even if they have the same symptoms you have. It may harm them.
You can ask your pharmacist or healthcare provider for information about TRADJENTA that is written for health professionals.

What are the ingredients in TRADJENTA?
Active Ingredient: linagliptin
Inactive Ingredients: copovidone, corn starch, magnesium stearate, mannitol, and pregelatinized starch. The film coating contains the following inactive ingredients: hypromellose, polyethylene glycol, red ferric oxide, talc, and titanium dioxide.

Distributed by: Boehringer Ingelheim Pharmaceuticals, Inc. Ridgefield, CT 06877 USA.
Licensed from: Boehringer Ingelheim International GmbH, Ingelheim, Germany.
TRADJENTA is a registered trademark of and used under license from Boehringer Ingelheim International GmbH.
Boehringer Ingelheim Pharmaceuticals, Inc. either owns or uses the CARMELINA® and CAROLINA® trademarks under license.
The other brands listed are trademarks of their respective owners and are not trademarks of Boehringer Ingelheim Pharmaceuticals, Inc.
Copyright © 2023 Boehringer Ingelheim International GmbH.
ALL RIGHTS RESERVED

Distributed By:

Cardinal Health

Dublin, OH 43017

ER7866 Rev. C

COL10194BF212023
For more information about TRADJENTA, including current prescribing information and Medication Guide, go to www.TRADJENTA.com, scan the code, or call Boehringer Ingelheim Pharmaceuticals, Inc. at 1-800-542-6257.

This Medication Guide has been approved by the U.S. Food and Drug Administration.

Revised: June 2023

Package/Label Display Panel

Contains Approximately

2640 Tablets

TRADJENTA®

(linagliptin) tablets

5 mg

Each tablet contains:

5 mg of linagliptin.

Dispense the Medication Guide to each

patient.

Rx Only

WARNING: Keep out of reach of

children.